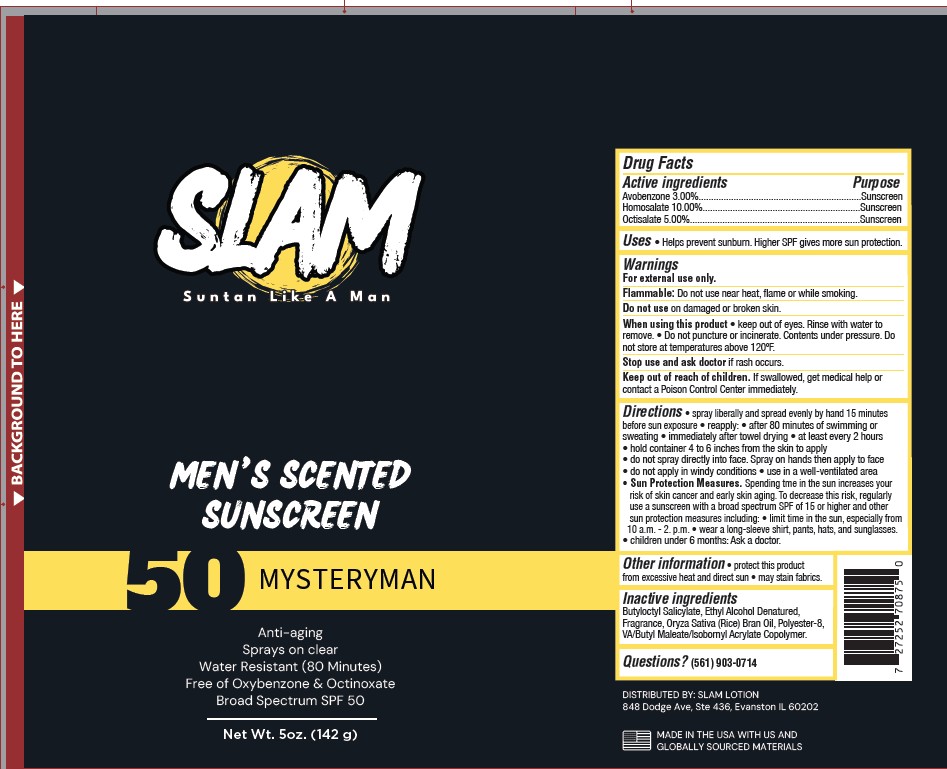 DRUG LABEL: Men scented sunscreen SPF 50 mysterman

NDC: 85943-005 | Form: SPRAY
Manufacturer: Slam Lotion
Category: otc | Type: HUMAN OTC DRUG LABEL
Date: 20250815

ACTIVE INGREDIENTS: AVOBENZONE 3 g/100 g; HOMOSALATE 10 g/100 g; OCTISALATE 5 g/100 g
INACTIVE INGREDIENTS: FRAGRANCE VERBENA JUNIPERBERRY ORC1403606; ORYZA SATIVA (RICE) BRAN; BUTYLOCTYL SALICYLATE; POLYESTER-8 (1400 MW, CYANODIPHENYLPROPENOYL CAPPED); ALCOHOL

SPF 50 Spray Mysterman

Active ingredients Purpose

Avobenzone 3.00% Sunscreen
Homosalate 10.00% Sunscreen
Octisalate 5.00%. Sunscreen

Uses

•helps prevent sunburn•

Warnings For external use only. Flammable:

Do not use near heat, flame or while smoking.

Do not use

on damaged or broken skin.

When using this product

• keep out of eyes. Rinse with water to remove. • Do not puncture or incinerate. Contents under pressure. Do not store at temperatures above 120ºF.

Stop use and ask doctor if

rash occurs.

Keep out of reach of children.

If swallowed, get medical help or contact a Poison Control Center immediately

Directions

• spray liberally and spread evenly by hand 15 minutes before sun exposure• reapply: • after 80 minutes of swimming or sweating • immediately after towel drying • at least every 2 hours

• hold container 4 to 6 inches from the skin to apply
• do not spray directly into face. Spray on hands then apply to face
• do not apply in windy conditions • use in a well-ventilated area
• Sun Protection Measures. Spending tme in the sun increases your risk of skin cancer and early skin aging.

To decrease this risk, regularly use a sunscreen with a broad spectrum SPF of 15 or higher and other sun protection measures including:

• limit time in the sun, especially from
10 a.m. - 2. p.m. • wear a long-sleeve shirt, pants, hats, and sunglasses.
• children under 6 months: Ask a doctor.

Inactive Ingredeints

Alcohol Denat.
Butyloctyl Salicylate
Fragrance
Oryza Sativa (Rice) Bran Oil
Polyester-8
VA/Butyl Maleate/Isobornyl Acrylate Copolymer